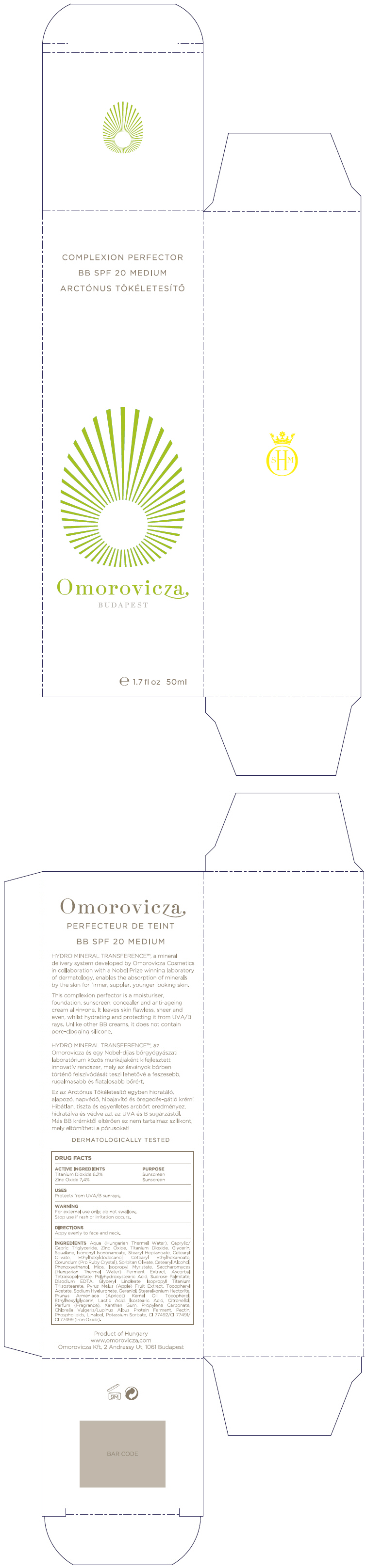 DRUG LABEL: Complexion Perfector BB SPF20 Medium
NDC: 41442-150 | Form: CREAM
Manufacturer: Omorovicza Kozmetikai Kft.
Category: otc | Type: HUMAN OTC DRUG LABEL
Date: 20130313

ACTIVE INGREDIENTS: Titanium Dioxide 62 mg/1 mL; Zinc Oxide 74 mg/1 mL
INACTIVE INGREDIENTS: Water; Caprylic/Capric Mono/Diglycerides; Glycerin; Squalane; Stearyl Heptanoate; Cetearyl Olivate; Cetearyl Ethylhexanoate; Aluminum Oxide; Sucrose Palmitate; Sorbitan Olivate; Cetostearyl Alcohol; Phenoxyethanol; Mica; Ascorbyl Tetraisopalmitate; Isononyl Isononanoate; Polyhydroxystearic Acid (2300 MW); Edetate Disodium; Glyceryl Monolinoleate; Apple; Isopropyl Myristate; .Alpha.-Tocopherol Acetate; Hyaluronate Sodium; Geraniol; Ethylhexylglycerin; Apricot Kernel Oil; Tocopherol; Lactic Acid; Glyceryl Isostearate; .Beta.-Citronellol, (+/-)-; Isopropyl Titanium Triisostearate; Xanthan Gum; Chlorella Vulgaris; Pectin; Omega-3 Fatty Acids; Linalool, (+)-; Potassium Sorbate; Stearalkonium Hectorite; Propylene Carbonate; Ferric Oxide Red

Complexion Perfector BB SPF20 Medium

DRUG FACTS

ACTIVE INGREDIENT

ACTIVE INGREDIENTS | PURPOSE
Titanium Dioxide 6.2% | Sunscreen
Zinc Oxide 7.4% | Sunscreen

USES

Protects from UVA/B sunrays.

WARNING

For external use only; do not swallow.

Stop use if rash or irritation occurs.

DIRECTIONS

Appy evenly to face and neck

INGREDIENTS

Aqua (Hungarian Thermal Water), Caprylic/Capric Triglyceride, Zinc Oxide, Titanium Dioxide, Glycerin, Squalane, Isononyl Isononanoate, Stearyl Heptanoate, Cetearyl Olivate, Ethylhexyldodecanol, Cetearyl Ethylhexanoate, Corundum (Pro Ruby Crystal), Sorbitan Olivate, Cetearyl Alcohol, Phenoxyethanol, Mica, Isopropyl Myristate, Saccharomyces (Hungarian Thermal Water) Ferment Extract, Ascorbyl Tetraisopalmitate, Polyhydroxystearic Acid, Sucrose Palmitate, Disodium EDTA, Glyceryl Linoleate, Isopropyl Titanium Triisostearate, Pyrus Malus (Apple) Fruit Extract, Tocopheryl Acetate, Sodium Hyaluronate, Geraniol, Stearalkonium Hectorite, Prunus Armeniaca (Apricot) Kernel Oil , Tocopherol, Ethylhexylglycerin, Lactic Acid, Isostearic Acid, Citronellol, Parfum (Fragrance), Xanthan Gum, Propylene Carbonate, Chlorella Vulgaris/Lupinus Albus Protein Ferment, Pectin, Phospholipids, Linalool, Potassium Sorbate, CI 77492/CI 77491/CI 77499 (Iron Oxide).

PRINCIPAL DISPLAY PANEL - 50ml Bottle Box

COMPLEXION PERFECTOR

BB SPF 20 MEDIUM

Omorovicza

BUDAPEST

e 1.7 fl oz 50ml